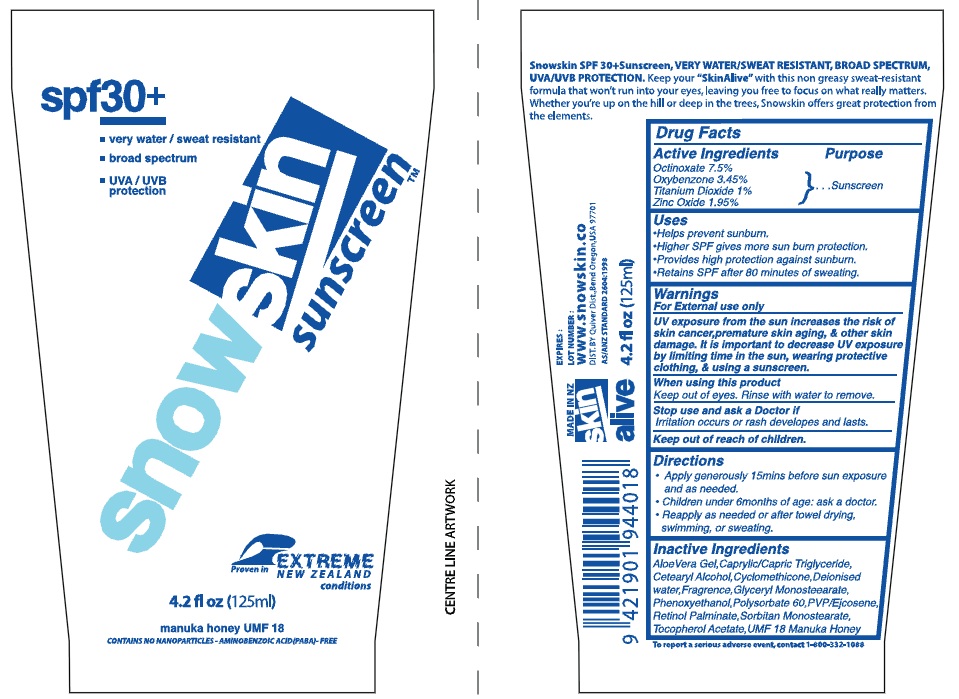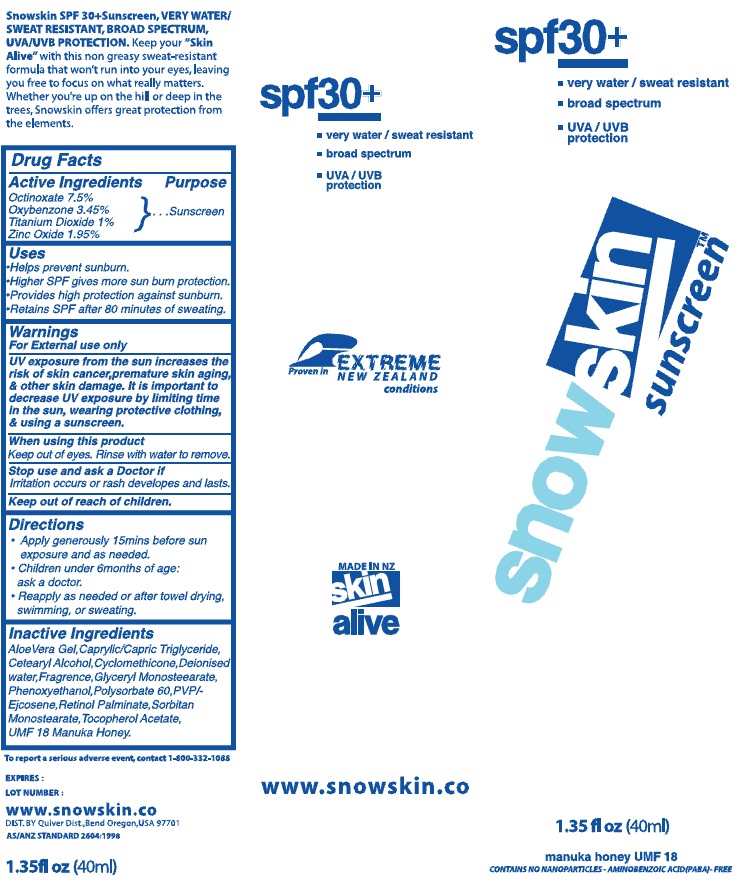 DRUG LABEL: SnowSkin Sunscreen
NDC: 75916-4018 | Form: CREAM
Manufacturer: Skin Alive, Ltd.
Category: otc | Type: HUMAN OTC DRUG LABEL
Date: 20110105

ACTIVE INGREDIENTS: OCTINOXATE 7.5 mL/100 mL; OXYBENZONE 3.45 mL/100 mL; TITANIUM DIOXIDE 1 mL/100 mL; ZINC OXIDE 1.95 mL/100 mL
INACTIVE INGREDIENTS: ALOE VERA LEAF; MEDIUM-CHAIN TRIGLYCERIDES; CETOSTEARYL ALCOHOL; CYCLOMETHICONE; WATER; GLYCERYL MONOSTEARATE; PHENOXYETHANOL; POLYSORBATE 60; VITAMIN A PALMITATE; SORBITAN MONOSTEARATE; ALPHA-TOCOPHEROL ACETATE

SNOWSKIN SUNSCREEN SPF 30+

Active Ingredients

Octinoxate, 7.5%

Oxybenzone, 3.45%

Titanium Dioxide, 1%

Zinc Oxide 1.95%

Purpose

Sunscreen

Uses

Helps prevent sunburn

Higher SPF gives more sunburn protection

Provides high protection against sunburn

Retains SPF after 80 minutes of sweating

Warnings

For external use only.

UV exposure fromt he sun increases the risk of skin cancer, premature skin aging, and other skin damage. It is important to decrease UV exposure by limiting time in the sun, wearing protective clothing, and using a sunscreen.

When using this product

Keep out of eyes. Rinse with water to remove.

Stop use and ask a doctor if

irritation occurs or rash develops and lasts.

Keep out of reach of children.

Directions

Apply generously 15mins before sun exposure and as needed.

Children under 6months of age: ask a doctor

Reapply as needed or after towel drying, swimming or sweating

Inactive Ingredients

Aloe Vera Gel, Caprylic/Capric Triglyceride, Cetearyl alcohol, Cyclomethicone, Deionised water, Fragrence, Glyceryl Monostearate, Phenoxyethanol, Polysorbate 60, PVP/Ejosene, Retinol Palmitate, Sorbitan Monostearate, Tocopherol Acetate, UMF 18 Manuka Honey

PACKAGE LABEL

spf30+

Very water/sweat resistant

broad spectrum

UVA/UVB

SNOWSKIN Sunscreen

Proven in Extreme New Zealand conditions

4.2 fl oz (125 ml)

manuka honey UMF 18

contains no nanoparticles - Aminobenzoic acid (PABA) Free

Snowskin SPF 30+ Sunscreen, Very water/sweat resistant, broad spectrum, UVA/UVB Protection. keep your "Skin alive" with this non-greasy sweat-resistant formula that won't run into your eyes, leaving you free to focus on what really matters. Whether you're up on the hill or deep in the trees, Snowskin offers great protection from the elements.

Expires:

Lot Number:

www.snowskin.co

DIST BY Quiver Dist., Bend Oregon, USA 97701

MADE IN NZ